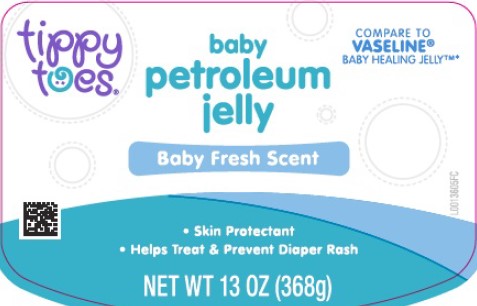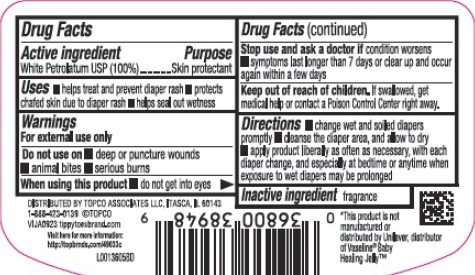 DRUG LABEL: Petroleum
NDC: 36800-519 | Form: JELLY
Manufacturer: Topco Associates LLC
Category: otc | Type: HUMAN OTC DRUG LABEL
Date: 20260213

ACTIVE INGREDIENTS: PETROLATUM 1 g/1 g

Top Care 519.001/519AE
Baby Petroleum Jelly

Active ingredient

White Petrolatum USP (100%)

Purpose

Skin Protectant

Uses

- helps treat and prevent diaper rash
- protects chafed skin due to diaper rash
- helps seal out wetness

Warnings

For external use only

Do not use on

- deep or puncture wounds
- animal bites
- serious burns

When using this product

- do not get into eyes

Stop use and ask a doctor

if condition worsens

- symptoms last longer than 7 days or clear up and occur again in a few days

Keep out of reach of children

If swallowed, get medical help or contact a Poison Control Center right away

Directions

- change wet and soilded diapers promptly
- cleanse the diaper area, and allow to dry
- apply product liberally as often as necessary, with each diaper change, and especially at bedtime or anytime when exposure to wet diapers may be prolonged

Inactive ingredient

fragrance

Disclaimer

*This product is not manufactured or distributed by Unilever, distributer of Vaseline® Baby Healing Jelly™

Adverse reaction

DISTRIBUTED BY TOPCO ASSOCIATES LLC, ITASCA, IL 60143

1-888-423-0139 ©TOPCO

VIJA0923 tippytoesbrand.com

Visit here for more information

Principal display panel

tippy toes®

COMPARE TO VASELINE® BABY HEALING JELLY™*

baby petroleum jelly

Baby Fresh Scent

- Skin Prtectant
- Helps Treat & Prevent Diaper Rash

NET WET 13 OZ (368 g)